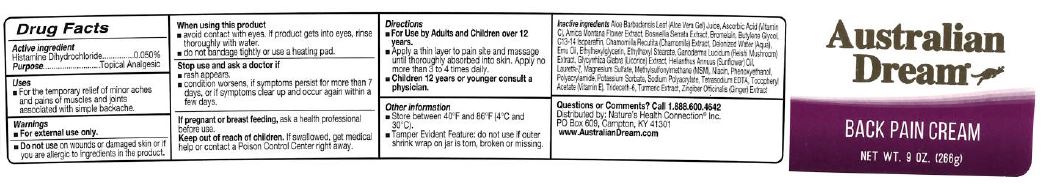 DRUG LABEL: Australian Dream Back Pain
NDC: 61577-8121 | Form: CREAM
Manufacturer: Sombra Cosmetics, Inc.
Category: otc | Type: HUMAN OTC DRUG LABEL
Date: 20240118

ACTIVE INGREDIENTS: HISTAMINE DIHYDROCHLORIDE .0005 g/1 g
INACTIVE INGREDIENTS: ALOE VERA LEAF; WATER; BUTYLENE GLYCOL; ARNICA MONTANA FLOWER; MATRICARIA CHAMOMILLA; EMU OIL; ETHYLHEXYLGLYCERIN; ETHYLHEXYL STEARATE; GLYCYRRHIZA GLABRA; SUNFLOWER OIL; C13-14 ISOPARAFFIN; ASCORBIC ACID; LAURETH-7; MAGNESIUM SULFATE, UNSPECIFIED; DIMETHYL SULFONE; EDETATE SODIUM TETRAHYDRATE; POLYACRYLAMIDE (10000 MW); POTASSIUM SORBATE; TURMERIC; GINGER; SODIUM POLYACRYLATE (8000 MW); TOCOPHEROL; TRIDECETH-6; GANODERMA LUCIDUM WHOLE; BOSWELLIA SERRATA WHOLE; BROMELAINS; NIACIN; PHENOXYETHANOL

Australian Dream Back Pain Cream

Active Ingredients

Histamine Dihydrochloride 0.05%

Keep out of reach of children

If swallowed, get medical help or contact a Poison Control Center right away

PURPOSE

Topical Analgesic

Uses

For temporary relief of minor aches and pains of muscles and joints associated with simple backache

Warnings

For external use only. Do not use on wounds or damaged skin or if you are allergic to ingredients in this product.

When using this product: avoid contact with eyes. If product gets into eyes, rinse thoroughly with water. Do not bandage tightly or use a heating pad.

Stop use and ask doctor if: rash appears. Condition worsens. If symptoms persist for more than 7 days or if symptoms clear up and occur again within a few days.

If pregnant or breast feeding, ask a health professional before use.

Directions

For Use by Adults and Children over 12 years. Apply a thin layer to pain site and massage until thoroughly absorbed into skin. Apply no more than 3 to 4 times daily.

Children 12 years or younger consult a physician

Inactive Ingredients

Aloe Barbadensis Leaf (Aloe Vera Gel), Aqua (Purified Water), Ascorbic Acid (Vitamin C), Arnica Montana Flower Extract, Boswellia Serrata Extract, Bromelain, Butylene Glycol, Chamomilla Recutita (Chamomile) Extract, Emu Oil, Ethylhexylglycerin, Ethylhexyl Stearate, Ganoderma Lucidum (Reishi Mushroom) Extract, Glycyrrhiza Glabra (Licorice) Extract, Helianthus Annuus (Sunflower) Seed Oil, C13-14 Isoparaffin, Laureth-7, Magnesium Sulfate, Methylsulfonylmethane (MSM), Niacin, Phenoxyethanol, Polyacrylamide, Potassium Sorbate, Sodium Polyacrylate, Tetrasodium EDTA, Tochopheryl Acetate (Vitamin E), Trideceth-6, Turmeric Extract, Zingiber Officinalis (Ginger) Extract

Questions or Comments?

Call 1-888-600-4642